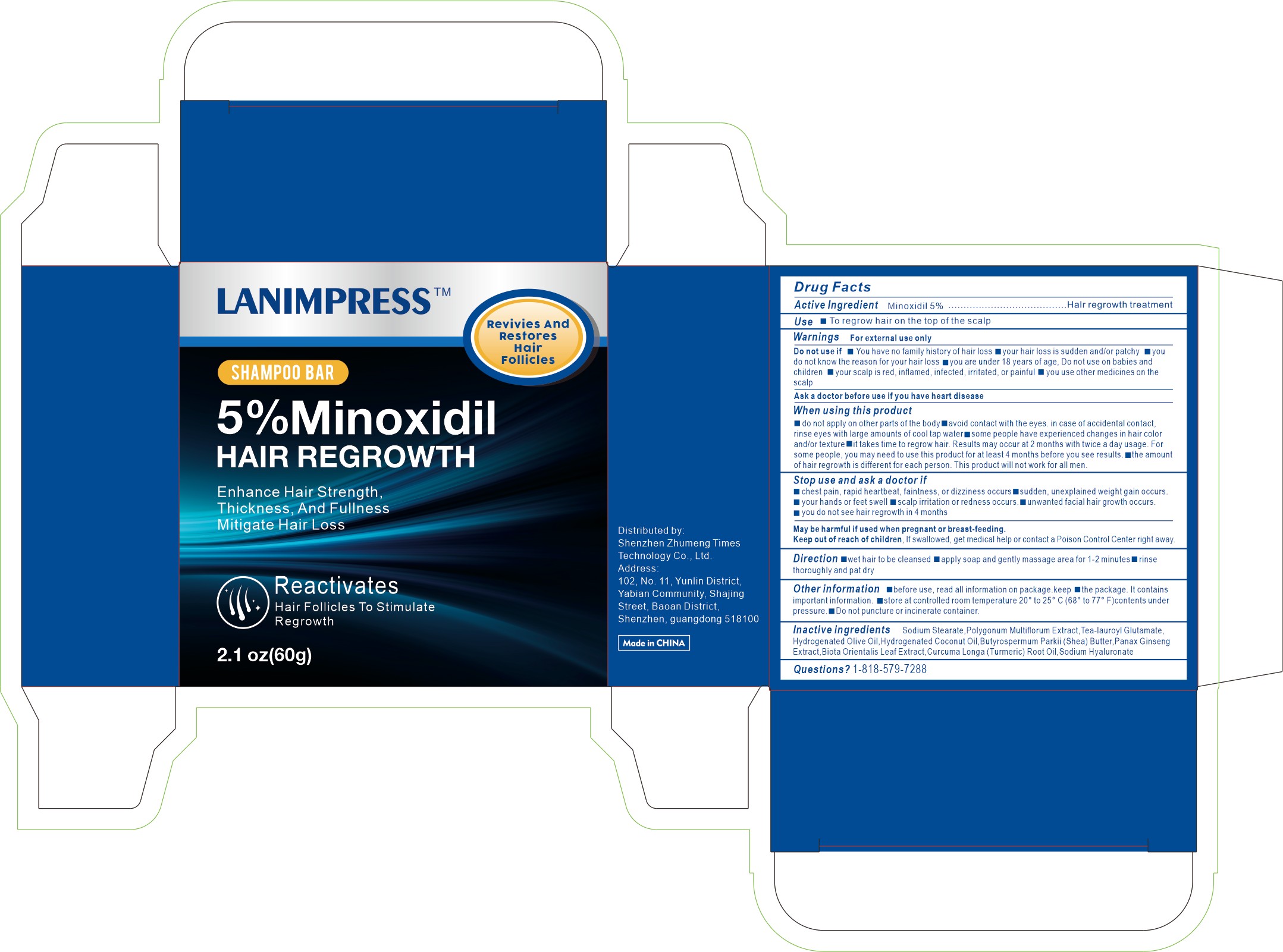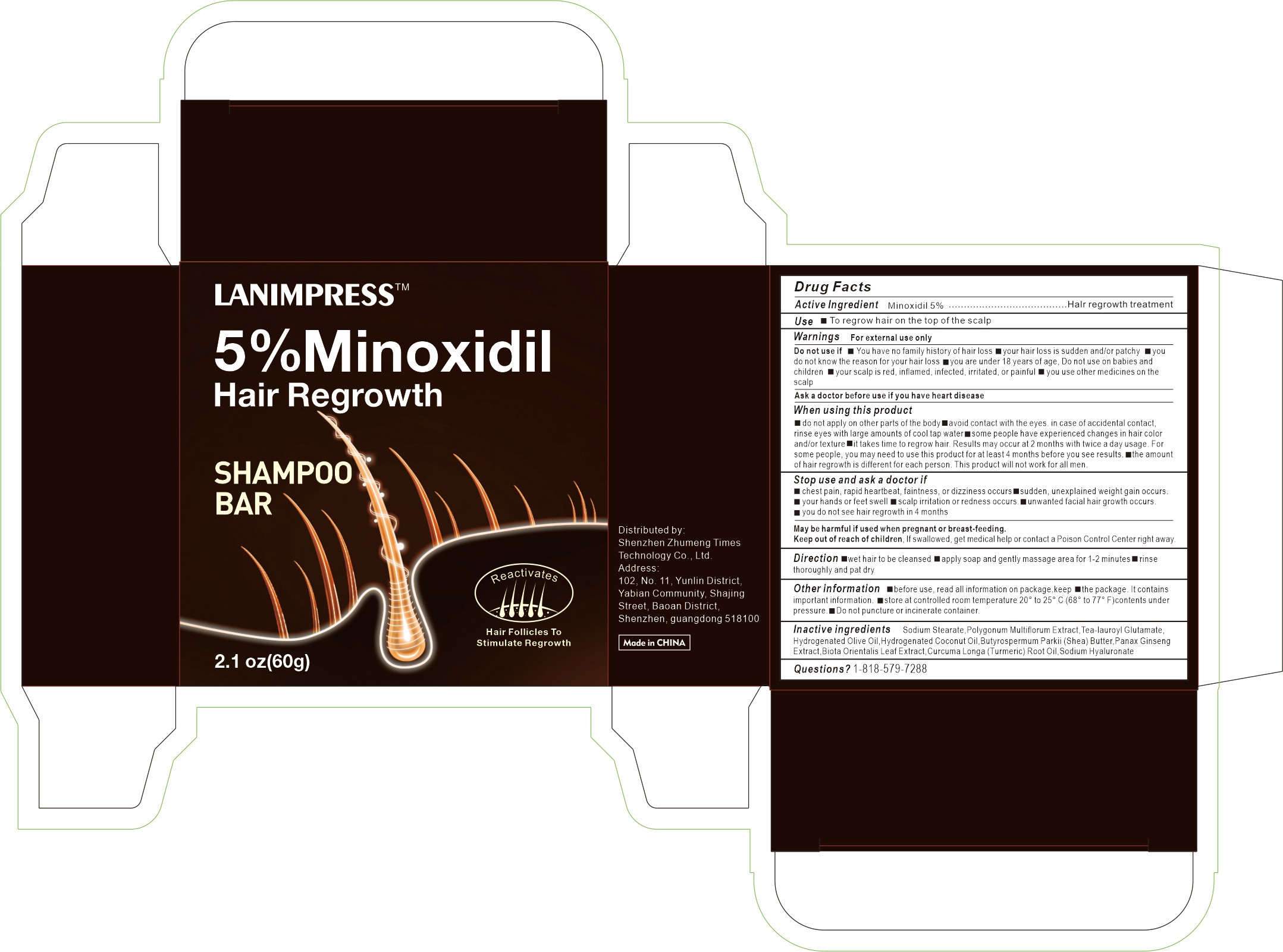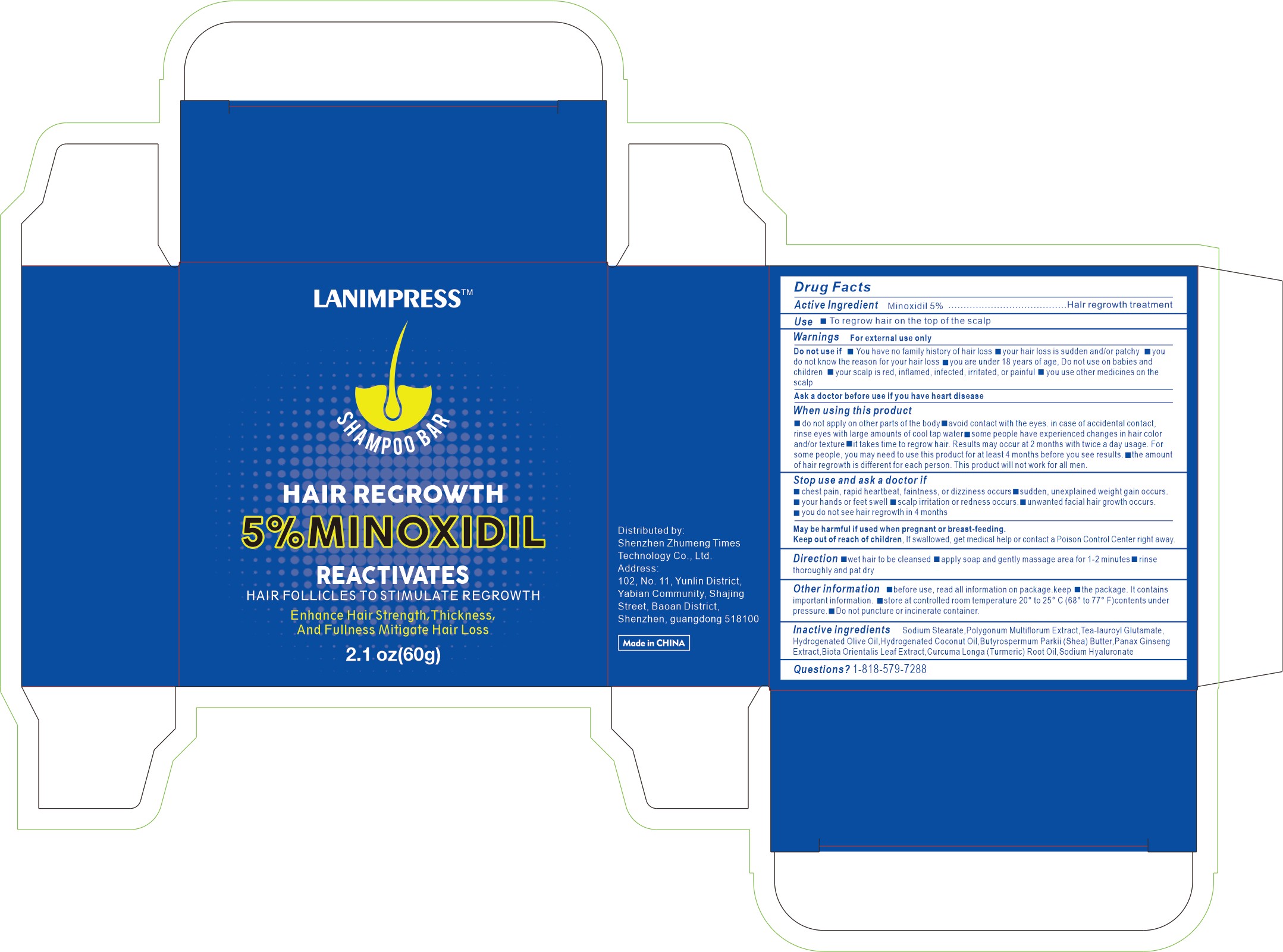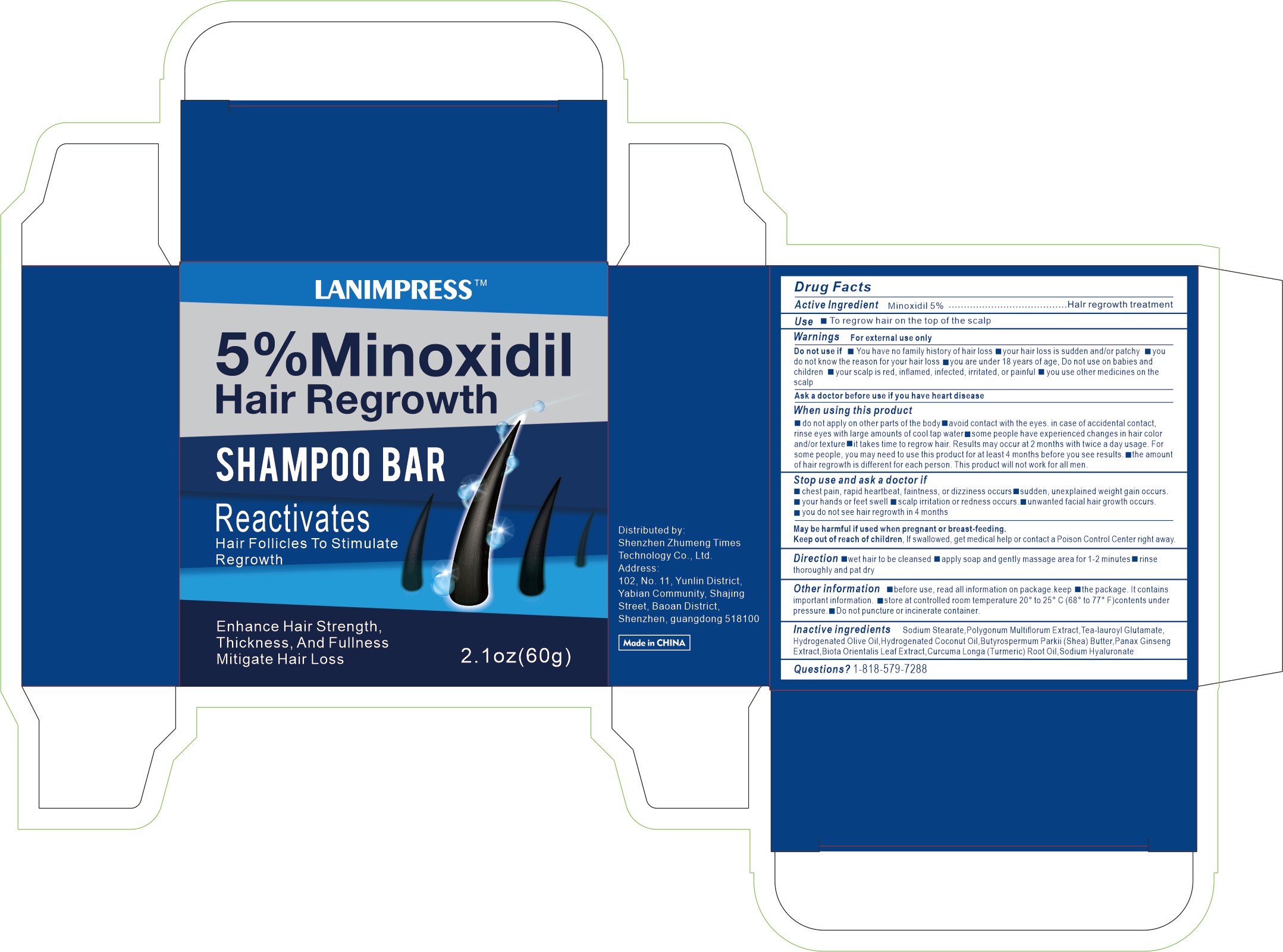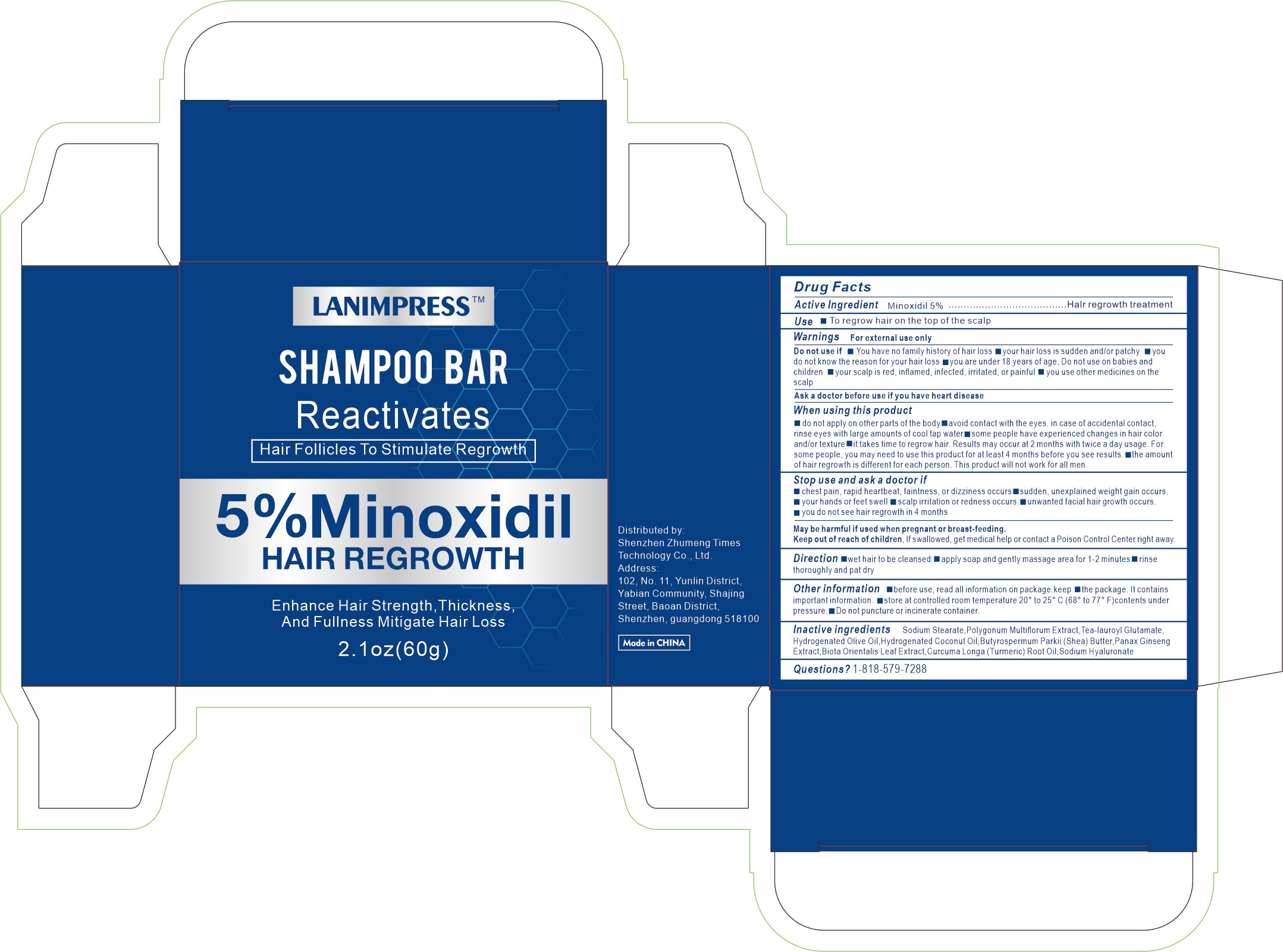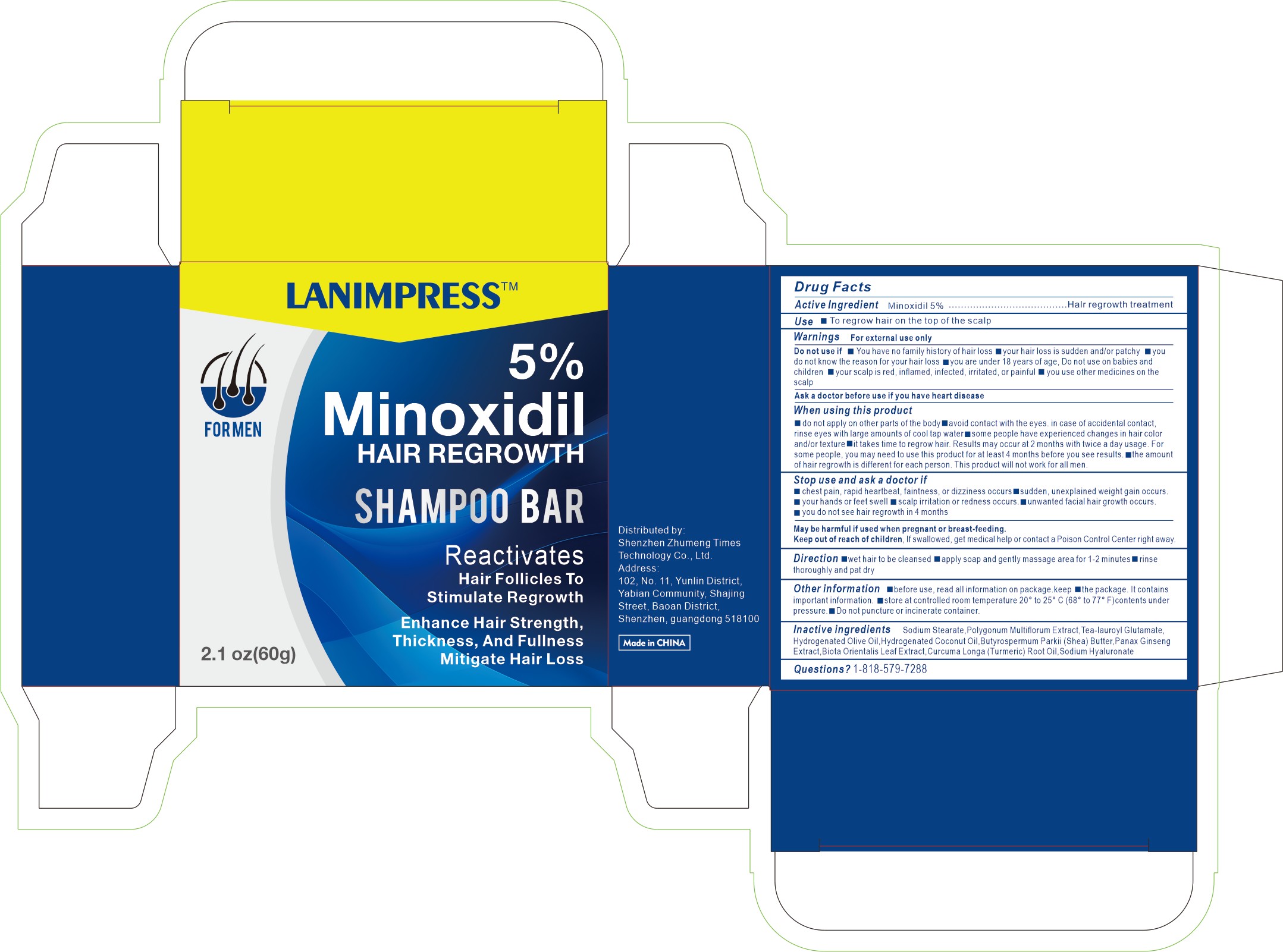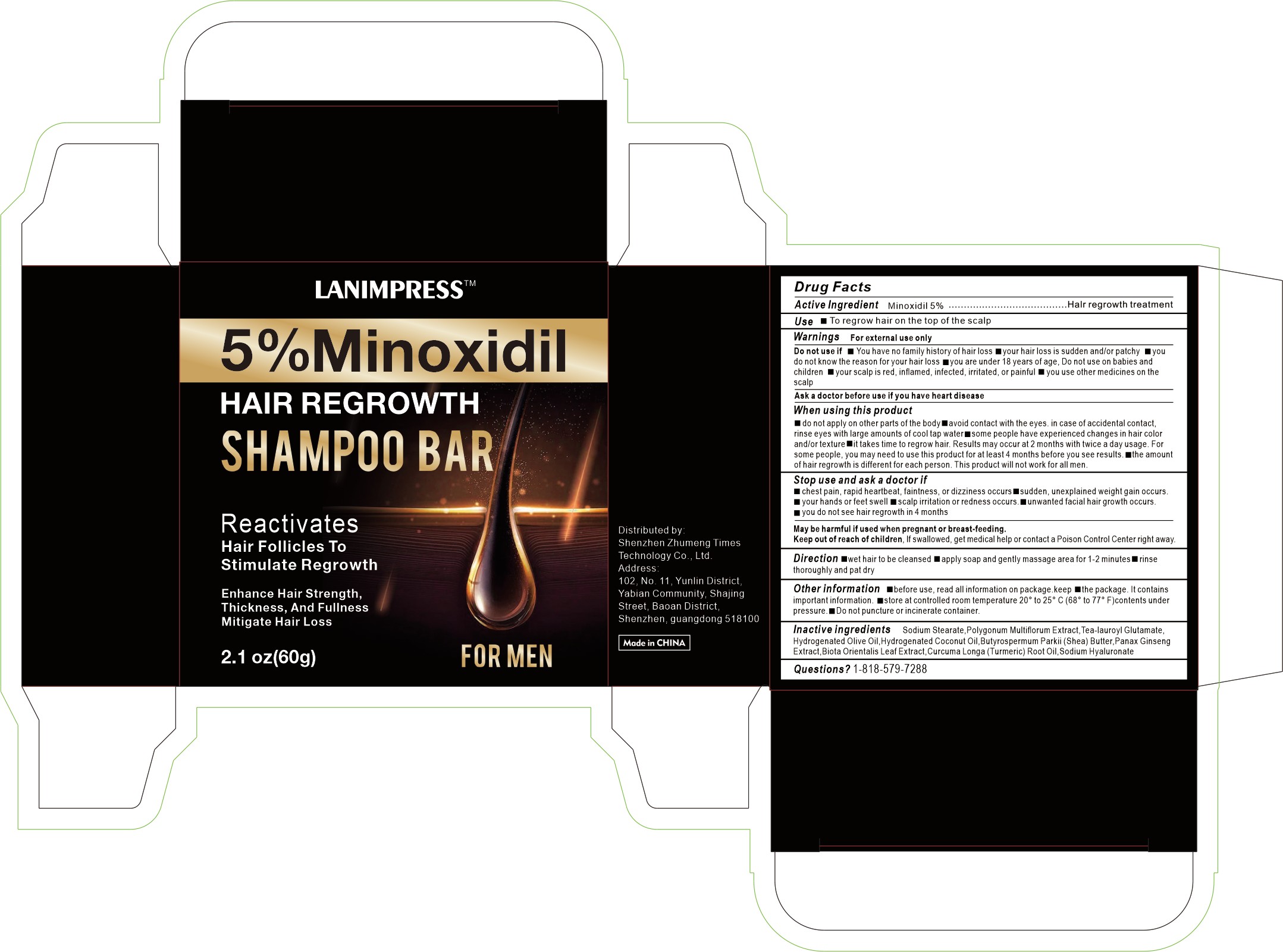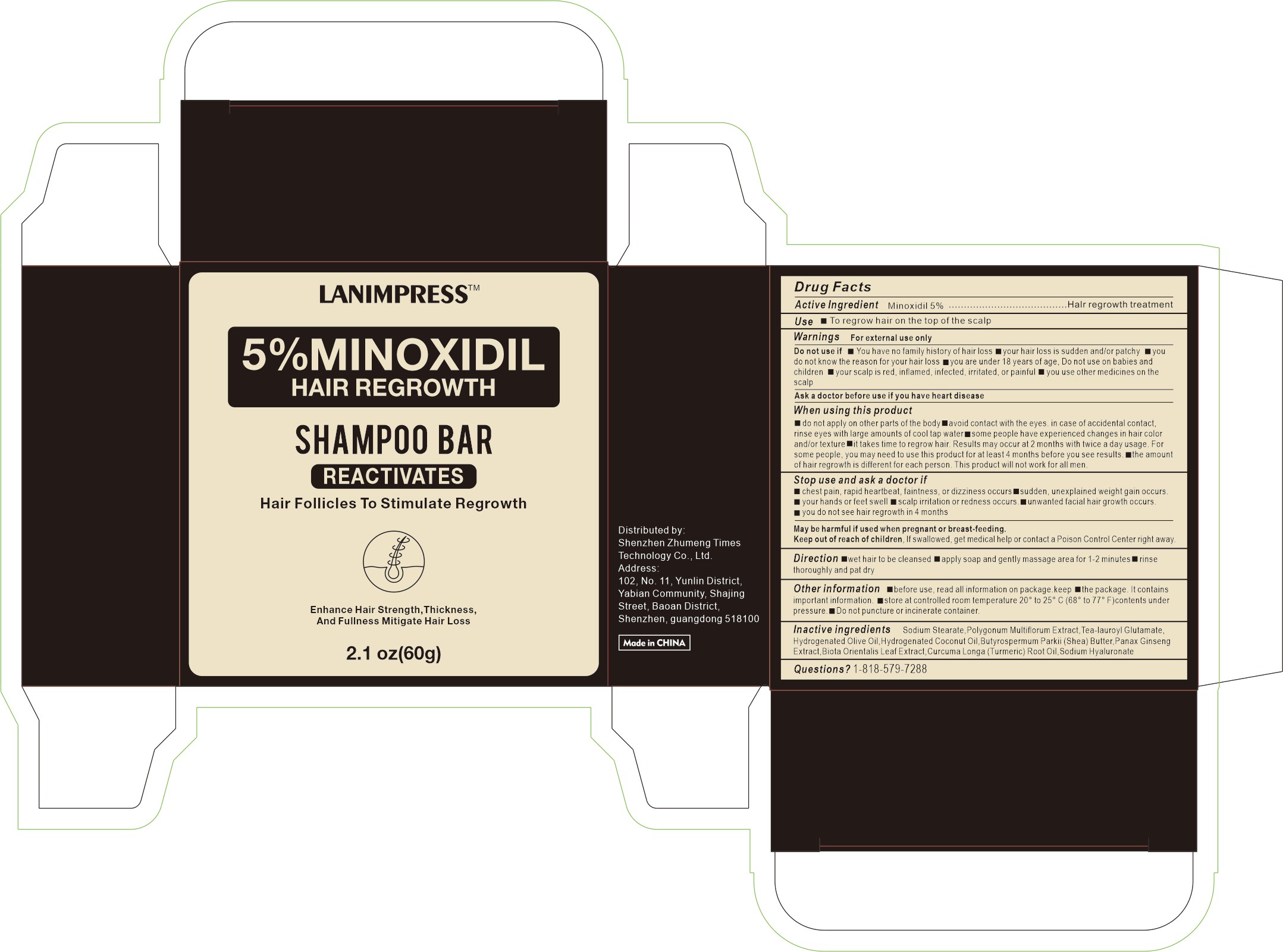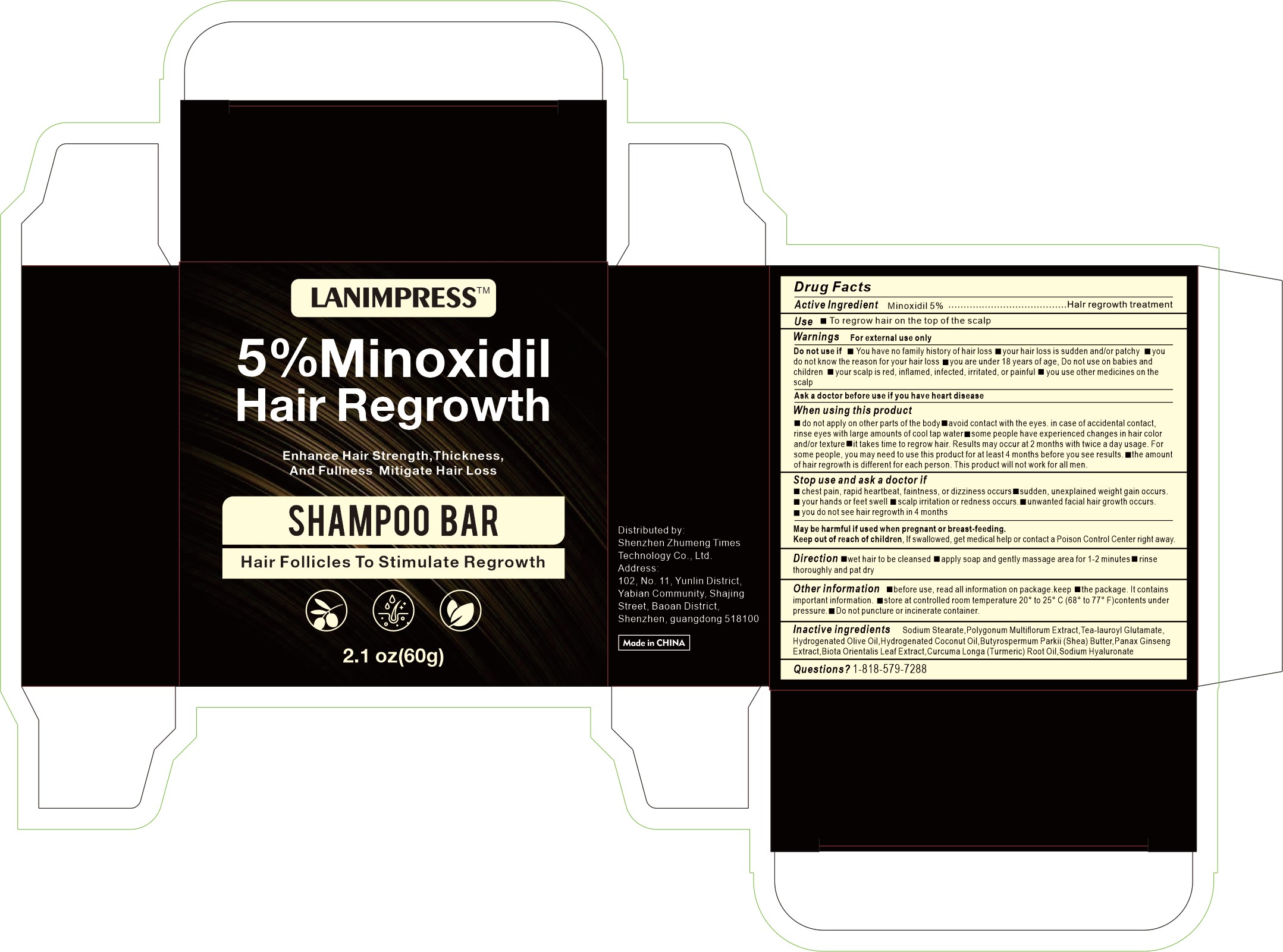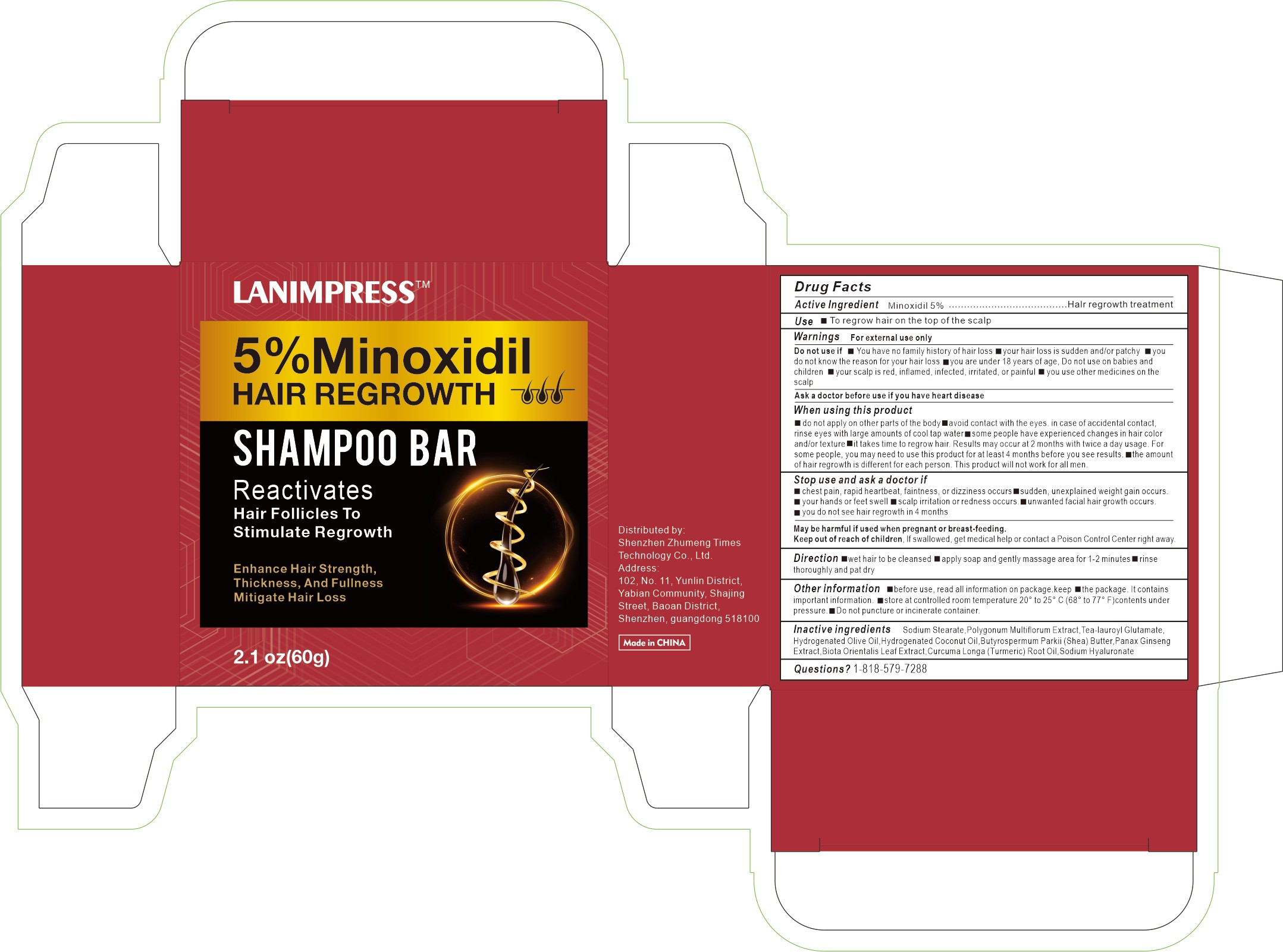 DRUG LABEL: 5%Minoxidil HAIR REGROWTH
NDC: 84778-022 | Form: SOAP
Manufacturer: Guangzhou Yixin Cross-border E-commerce Co., Ltd.
Category: otc | Type: HUMAN OTC DRUG LABEL
Date: 20241102

ACTIVE INGREDIENTS: MINOXIDIL 5 g/5 g
INACTIVE INGREDIENTS: PANAX GINSENG ROOT OIL; CURCUMA LONGA (TURMERIC) ROOT OIL; HYDROGENATED OLIVE OIL; SODIUM STEARATE; TEA-LAUROYL GLUTAMATE; PLATYCLADUS ORIENTALIS LEAF; POLYGONUM MULTIFLORUM ROOT EXTRACT; BUTYROSPERMUM PARKII (SHEA) BUTTER; HYDROGENATED COCONUT OIL; SODIUM HYALURONATE

COMPONENTS

Minoxidi 5g

PURPOSE

To regrow hair on the top of the scal

INDICATIONS AND USAGE

Open the box and take out the product

Do not use if your scalp is inflamed, red, or allergic.

DOSAGE AND ADMINISTRATION

For external use only.

DO NOT USE

You have no family history of hair lossyour hair loss is sudden and/or patchyyou do not know the reason for your hair loss you are under 18 years of age, Do not use on babies and children your scalp is red, inflamed, infected, irritated, or painful you use other medicines on the scalpDo not use if

Keep out of reach of children and pets.

Do not use this box incribs,beds,carriages or play pens,This Product is not a TOY.

INACTIVE INGREDIENT

Sodium Stearate

Polygonum Multiflorum Extract

Tea-lauroyl Glutamate

Hydrogenated Olive Oil

Hydrogenated Coconut Oil

Butyrospermum Parkii (Shea) Butter

Panax Ginsen Extract

Biota Orientalis Leaf Extract

Curcuma Longa (Turmeric) Root Oil

Sodium Hyaluronat